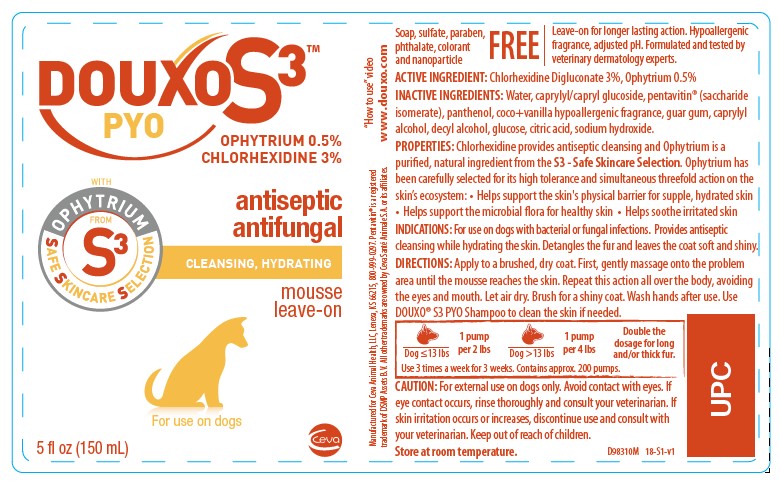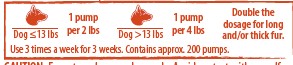 DRUG LABEL: DOUXO S3
NDC: 13744-153 | Form: LIQUID
Manufacturer: Ceva Sante Animale
Category: animal | Type: OTC ANIMAL DRUG LABEL
Date: 20250312

ACTIVE INGREDIENTS: OPHIOPOGON JAPONICUS ROOT 5.0 mg/1 mL; CHLORHEXIDINE 30 mg/1 mL
INACTIVE INGREDIENTS: CAPRYLYL/CAPRYL OLIGOGLUCOSIDE; SACCHARIDE ISOMERATE; GUAR GUM; CAPRYLYL GLYCOL; DECYL ALCOHOL; ANHYDROUS DEXTROSE; CITRIC ACID MONOHYDRATE; SODIUM HYDROXIDE

DOUXO S3™ PYO

OPHYTRIUM 0.5%

CHLORHEXIDINE 3%

Soap, sulfate, paraben, phthalate, colorant and nanoparticle FREE

Leave-on for longer lasting action. Hypoallergenic fragrance, adjusted pH. Formulated and tested by veterinary dermatology experts.

ACTIVE INGREDIENT: Chlorhexidine Digluconate 3%, Ophytrium 0.5%

INACTIVE INGREDIENT

INACTIVE INGREDIENTS: Water, caprylyl/capryl glucoside, pentavitin® (saccharide isomerate), panthenol, coco+vanilla hypoallergenic fragrance, guar gum, caprylyl alcohol, decyl alcohol, glucose, citric acid, sodium hydroxide.

DESCRIPTION

PROPERTIES: Chlorhexidine provides antiseptic cleansing and Ophytrium is a purified, natural ingredient from the S3 - Safe Skincare Selection. Ophytrium has been carefully selected for its high tolerance and simultaneous threefold action on the skin’s ecosystem: • Helps support the skin's physical barrier for supple, hydrated skin • Helps support the microbial flora for healthy skin • Helps soothe irritated skin

INDICATIONS AND USAGE

INDICATIONS: For use on dogs with bacterial or fungal infections. Provides antiseptic cleansing while hydrating the skin. Detangles the fur and leaves the coat soft and shiny.

DIRECTIONS: Apply to a brushed, dry coat. First, gently massage onto the problem area until the mousse reaches the skin. Repeat this action all over the body, avoiding the eyes and mouth. Let air dry. Brush for a shiny coat. Wash hands after use. Use DOUXO® S3 PYO Shampoo to clean the skin if needed.

PRECAUTIONS

CAUTION: For external use on dogs only. Avoid contact with eyes. If eye contact occurs, rinse thoroughly and consult your veterinarian. If
skin irritation occurs or increases, discontinue use and consult with your veterinarian. Keep out of reach of children.

STORAGE AND HANDLING

Store at room temperature.

“How to use” video www.douxo.com

Manufactured for Ceva Animal Health, LLC, Lenexa, KS 66215, 800-999-0297
Pentavitin® is a registered trademark of DSMP Assets B.V.
All other trademarks are owned by Ceva Santé Animale S.A. or its affiliates.

PRINCIPAL DISPLAY PANEL - 150 mL Bottle

DOUXO S3™

PYO

OPHYTRIUM 0.5%

CHLORHEXIDINE 3%

antiseptic

antifungal

CLEANSING, HYDRATING

mousse leave-on

For use on dogs or cats

5 fl oz (150 mL)